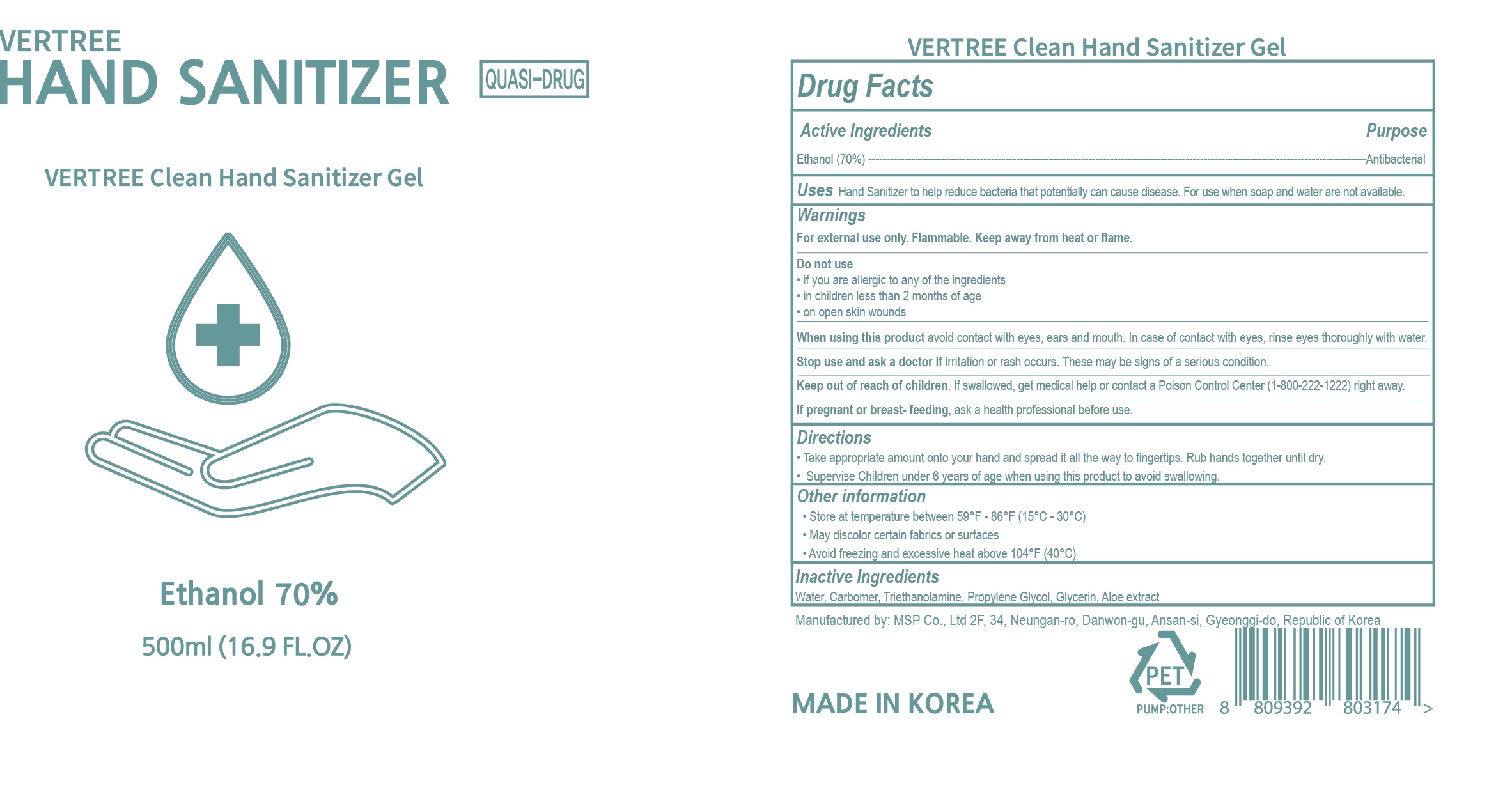 DRUG LABEL: VERTREE Clean Hand Sanitizer Gel
NDC: 77949-101 | Form: GEL
Manufacturer: MSP CO., LTD.
Category: otc | Type: HUMAN OTC DRUG LABEL
Date: 20200526

ACTIVE INGREDIENTS: ALCOHOL 70 mL/100 mL
INACTIVE INGREDIENTS: ALOE; CUPRIC BIS(TRIETHANOLAMINE); CARBOMER HOMOPOLYMER, UNSPECIFIED TYPE; WATER; GLYCERIN

VERTREE Hand Sanitizer Gel (Ethanol 70%, 500mL)

Active ingredient

Ethanol 70%

Uses

Hand sanitizer to help reduce bacteria that potentially can cause disease. For use when soap and water are not available.

Purpose

Antibacterial

Warnings

For external use only. Flammable. Keep away from heat or flame.

Do not use

- if you are allergic to any of the ingredients
- in children less than 2 months of age
- on open skin wounds

When using this product avoid contact with eyes., ears and mouth. In case of contact with eyes, rinse eyes thoroughly with water

Stop use and ask a doctor if irritation or rash occurs. These may be signs of a serious condition.

If pregnant or breast-feeding, ask a health professional before use.

Directions

- Take appropriate amount onto your hand and spread it all the way to fingertips. Rub hands together until dry.
- Supervise children under 6 years of age when using this product to avoid swallowing.

Other Information

Store at temperature between 59F ~ 86F (15C ~ 30C)

May discolor certain fabrics or surfaces

Avoid freezing and excessive heat above 104F (40C)